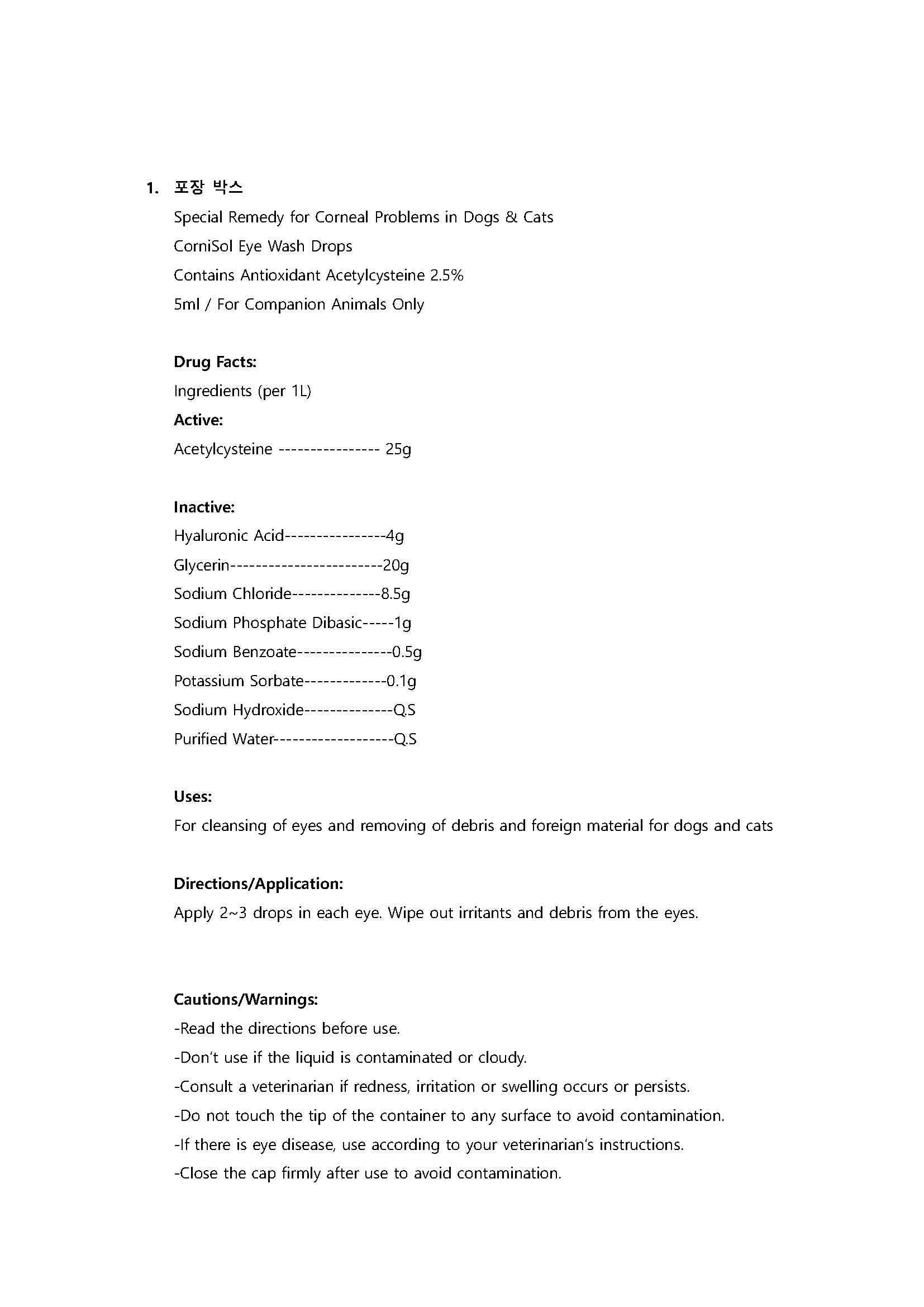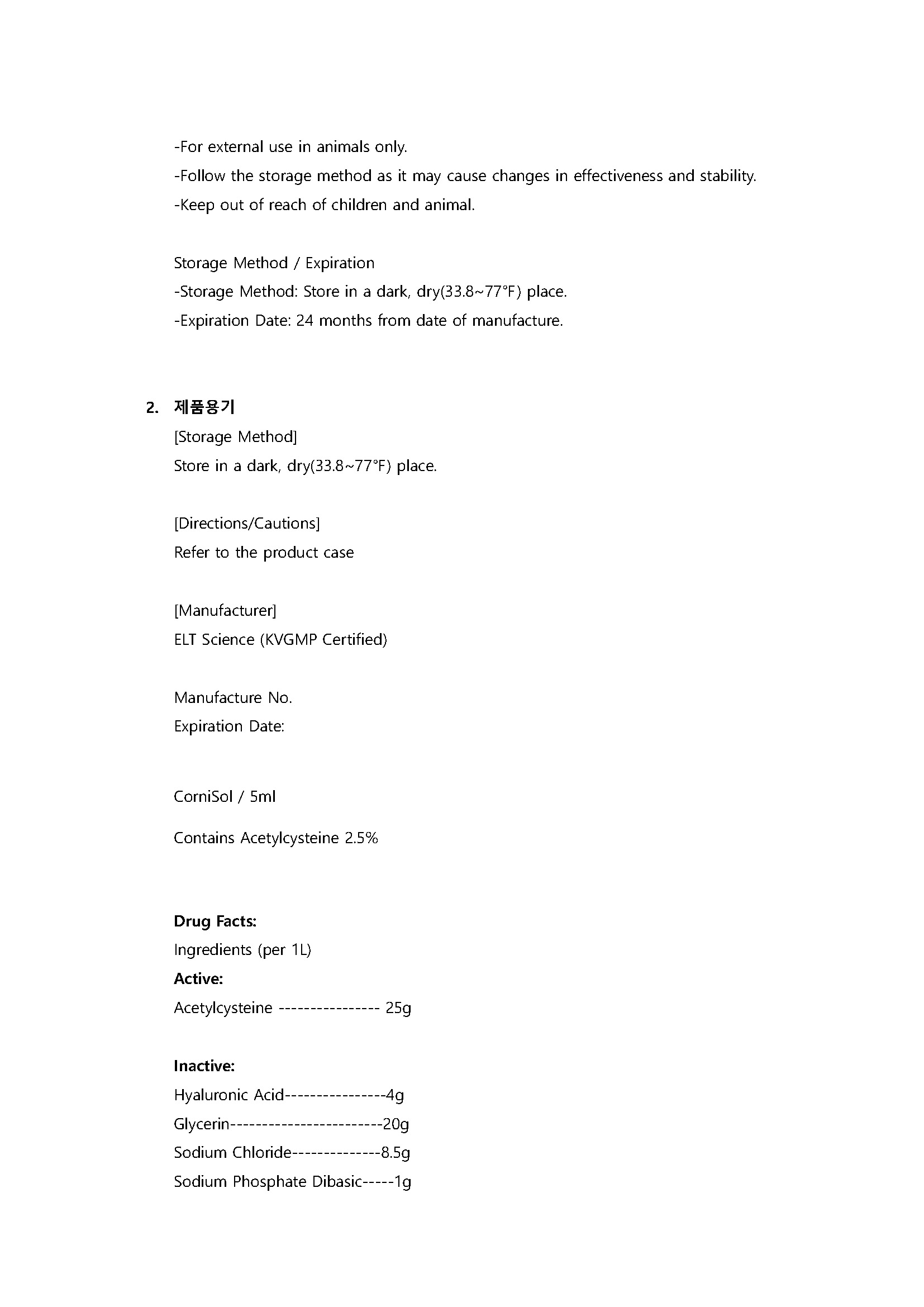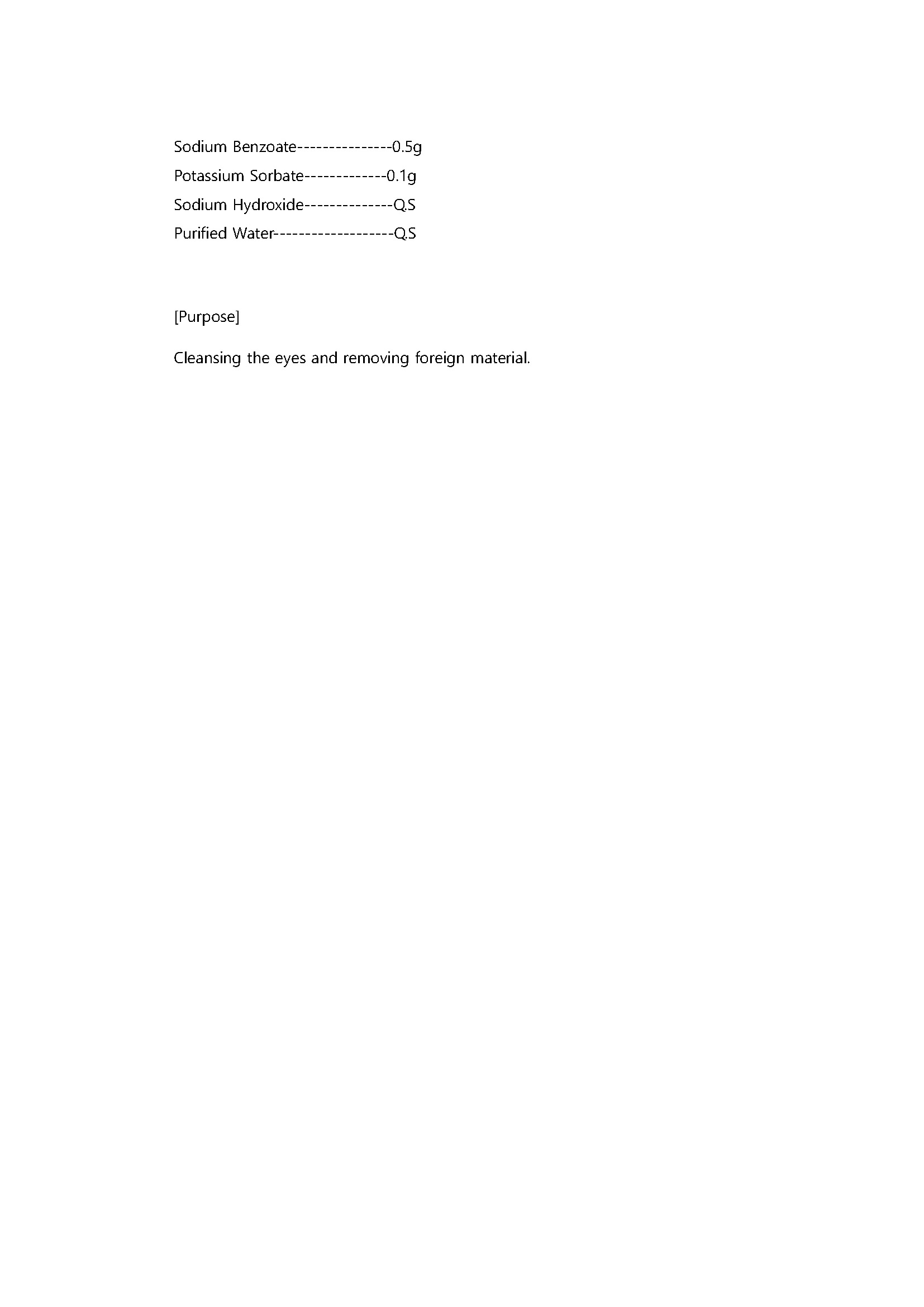 DRUG LABEL: CorniSol Eye Wash Drops
NDC: 86200-0003 | Form: SOLUTION/ DROPS
Manufacturer: ELT SCIENCE CORP
Category: animal | Type: OTC ANIMAL DRUG LABEL
Date: 20240927

ACTIVE INGREDIENTS: ACETYLCYSTEINE 2.5 g/100 mL
INACTIVE INGREDIENTS: SODIUM CHLORIDE; GLYCERIN

ACTIVE INGREDIENT

Acetylcysteine

INACTIVE INGREDIENT

Hyaluronic Acid----------------4g
Glycerin------------------------20g
Sodium Chloride--------------8.5g
Sodium Phosphate Dibasic-----1g
Sodium Benzoate---------------0.5g
Potassium Sorbate-------------0.1g
Sodium Hydroxide--------------Q.S
Purified Water-------------------Q.S

PURPOSE

For cleansing of eyes and removing of debris and foreign material for dogs and cats

Keep out of reach of children

INDICATIONS AND USAGE

Apply 2~3 drops in each eye. Wipe out irritants and debris from the eyes.

WARNINGS

-Read the directions before use.
-Don’t use if the liquid is contaminated or cloudy.
-Consult a veterinarian if redness, irritation or swelling occurs or persists.
-Do not touch the tip of the container to any surface to avoid contamination.
-If there is eye disease, use according to your veterinarian’s instructions.
-Close the cap firmly after use to avoid contamination.
-For external use in animals only.
-Follow the storage method as it may cause changes in effectiveness and stability.
-Keep out of reach of children and animal.

Storage Method / Expiration
-Storage Method: Store in a dark, dry(33.8~77℉) place.
-Expiration Date: 24 months from date of manufacture.

DOSAGE AND ADMINISTRATION

For external use only